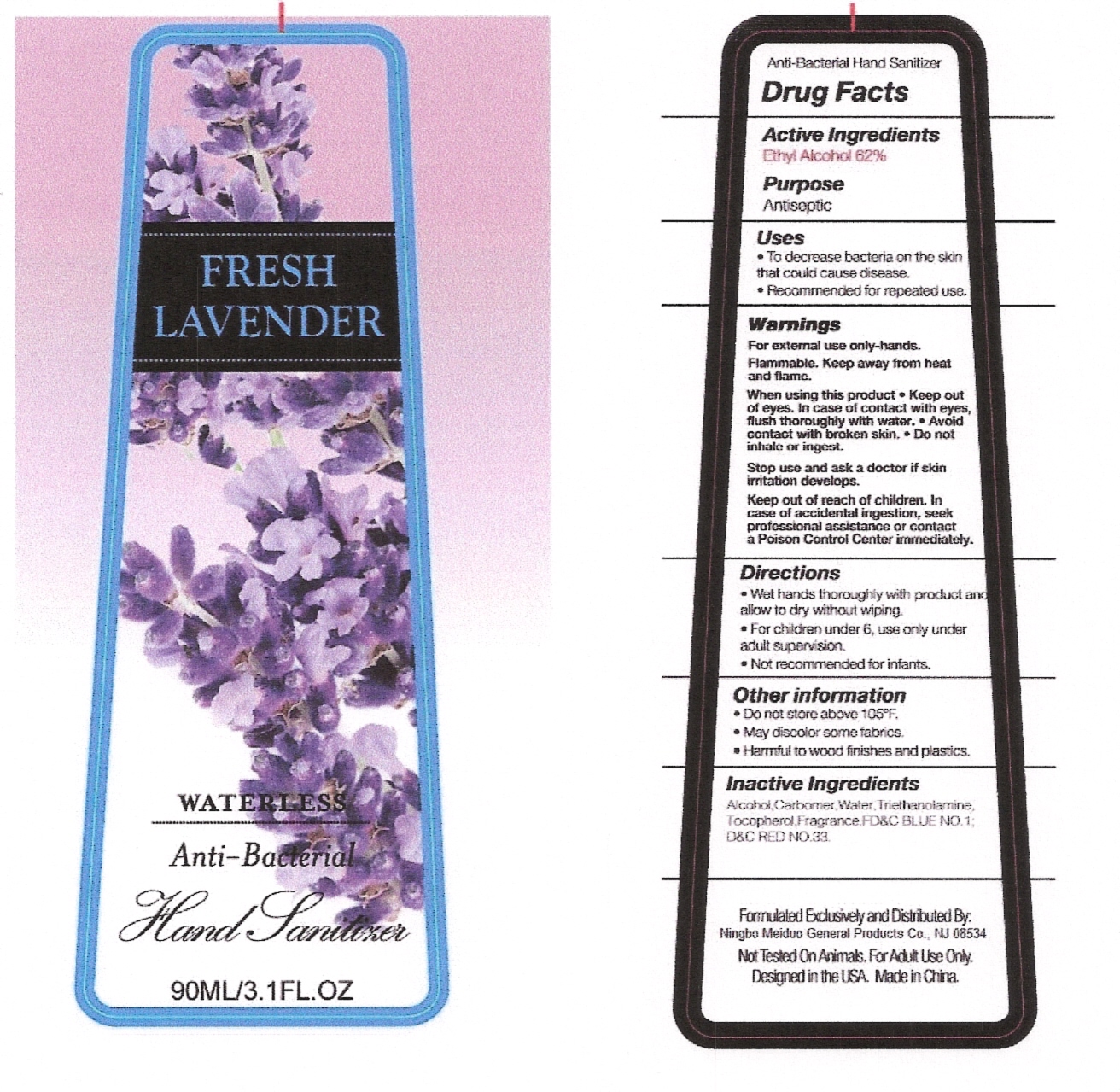 DRUG LABEL: Fresh Lavender Waterless Anti-Antibateria Hand Sanitizer
NDC: 22100-021 | Form: LIQUID
Manufacturer: NINGBO MEIDUO GENERAL PRODUCTS CO., LTD
Category: otc | Type: HUMAN OTC DRUG LABEL
Date: 20110508

ACTIVE INGREDIENTS: ALCOHOL 62 g/100 g
INACTIVE INGREDIENTS: WATER 37.19985 g/100 g; CARBOMER COPOLYMER TYPE A; TROLAMINE; ALPHA-TOCOPHEROL; D&C RED NO. 33; LAVENDER OIL; FD&C BLUE NO. 1

Drug Fact

Active Ingredient

Ethyl Alcohol 62%

Purpose

Antiseptic

INDICATIONS AND USAGE

For External Use Only- Hands

WARNINGS

Flammable: Keep away from heat and flame

When using this product: Keep out of eyes. In case of contact with eyes, flush thoroughly with water. Do not inhale or ingest. Avoid Contact with broken skin.

Stop use and ask a doctor if skin irritation develops

Keep out of reach of children. In case of accidental ingestion, seek professional assistance or contact a Poison Control Center immediately

Directions

- Wet hands thoroughly with product and allow to dry without wiping
- For children under 6, use only under adult supervision
- Not recommended for infants

Other Information:

- Do not store above 105F
- May discolor some fabrics
- Harmful to wood finishes and plastics

Inactive Ingredient:

Carbomer, Water, Triethanolamine, Fragrance, Tocopherol, FD and C Blue No. 1, D and C Red No. 33.

PACKAGE LABEL

labe